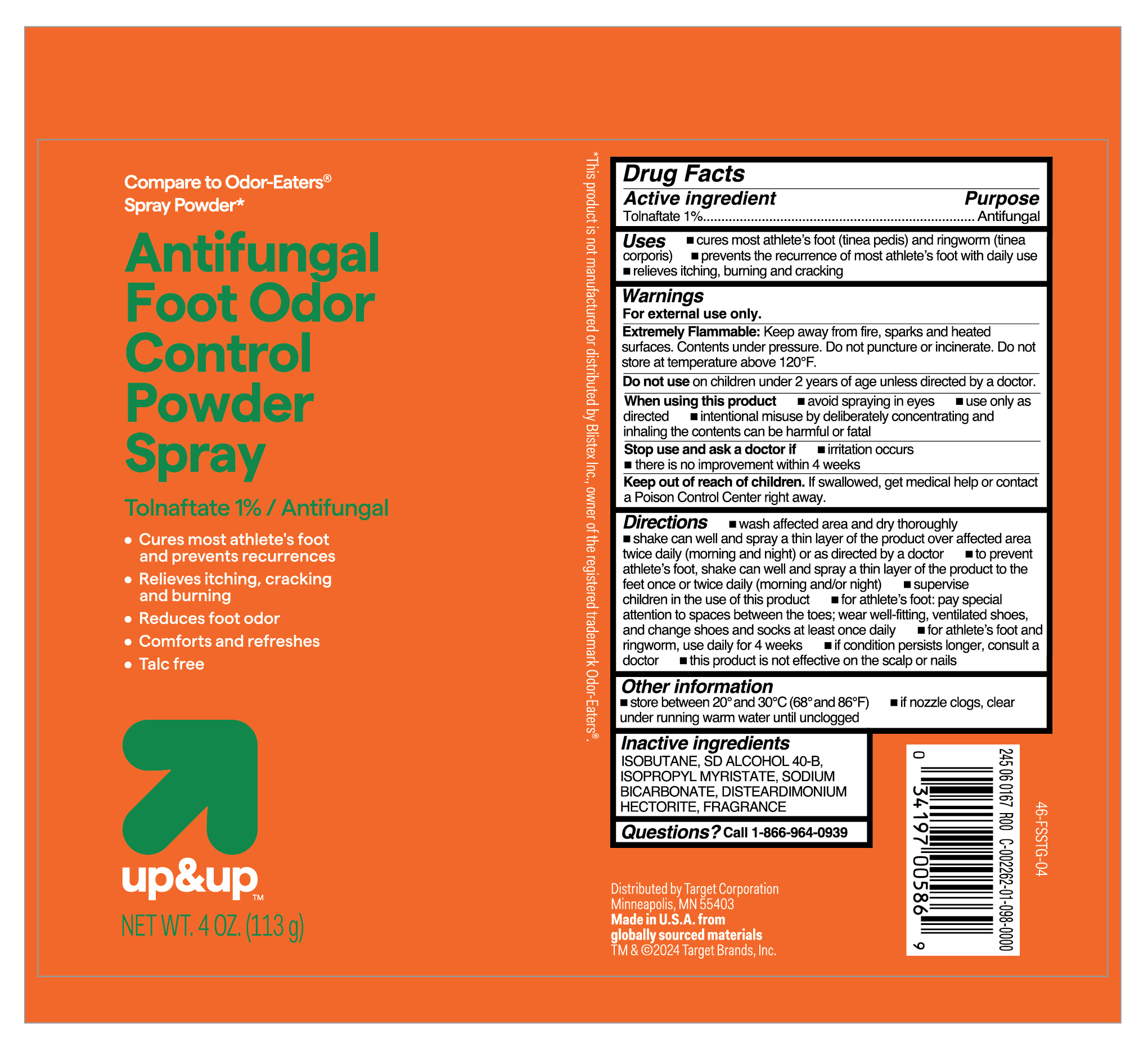 DRUG LABEL: Tolnaftate
NDC: 82442-402 | Form: AEROSOL, POWDER
Manufacturer: Target Corporation
Category: otc | Type: HUMAN OTC DRUG LABEL
Date: 20251106

ACTIVE INGREDIENTS: TOLNAFTATE 10 mg/1 g
INACTIVE INGREDIENTS: DISTEARDIMONIUM HECTORITE; ISOBUTANE; ISOPROPYL MYRISTATE; ALCOHOL; SODIUM BICARBONATE

Target Antifungal Foot Odor Control Powder Spray

Active ingredient

Tolnaftate 1%

Purpose

Antifungal

Uses

- cures most athlete's foot (tinea pedis) and ringworm (tinea corporis)
- prevents the recurrence of most athlete's foot with daily use
- relieves itching, burning and cracking

Warnings

For external use only.

Extremely Flammable:

Keep away from fire, sparks and heated surfaces. Contents under pressure. Do not puncture or incinerate. Do not store at temperature above 120ºF.

Do not use

on children under 2 years of age unless directed by a doctor.

When using this product

- avoid spraying in eyes
- use only as directed
- intentional misuse by deliberately concentrating and inhaling the contents can be harmful or fatal.

Stop use and ask a doctor if

- irritation occurs
- there is no improvement within 4 weeks

Keep out of reach of children.

If swallowed, get medical help or contact a Poison Control Center right away.

Directions

- wash affected area and dry thoroughly
- shake can well and spray a thin layer of the product over affected area twice daily (morning and night) or as directed by a doctor
- to prevent athlete's foot, shake can well and spray a thin layer of the product to the feet once or twice daily (morning and/or night)
- supervise children in the use of this product
- for athlete's foot: pay special attention to spaces between the toes, wear well-fitting, ventilated shoes, and change shoes and socks at least once daily
- for athlete's foot and ringworm, use daily for 4 weeks
- if conditions persist longer, consult a doctor
- this product is not effective on the scalp or nails

Other information

- store between 20º and 30ºC (68ºF and 86º)
- if nozzle clogs, clear under running warm water until unclogged

Inactive ingredient

ISOBUTANE, SD ALCOHOL 40-B, ISOPROPYL MYRISTATE, SODIUM BICARBONATE, DISTEARDIMONIUM HECTORITE, FRAGRANCE,

Questions?

Call 1-866-964-0939

RECENT MAJOR CHANGES

.

Principal Display Panel

Compare to Odor -Eaters

Spray Powder

Antifungal

Foot Odor

Control

Powder

Spray

Tolnaftate 1% / Antifungal

- Cures most athlete's foot

and prevents recurrences

- Relieves itching, cracking

and burning

- Reduces foot odor
- Comforts and refreshes
- Talc free

NET WT. 4 OZ. (113 g)